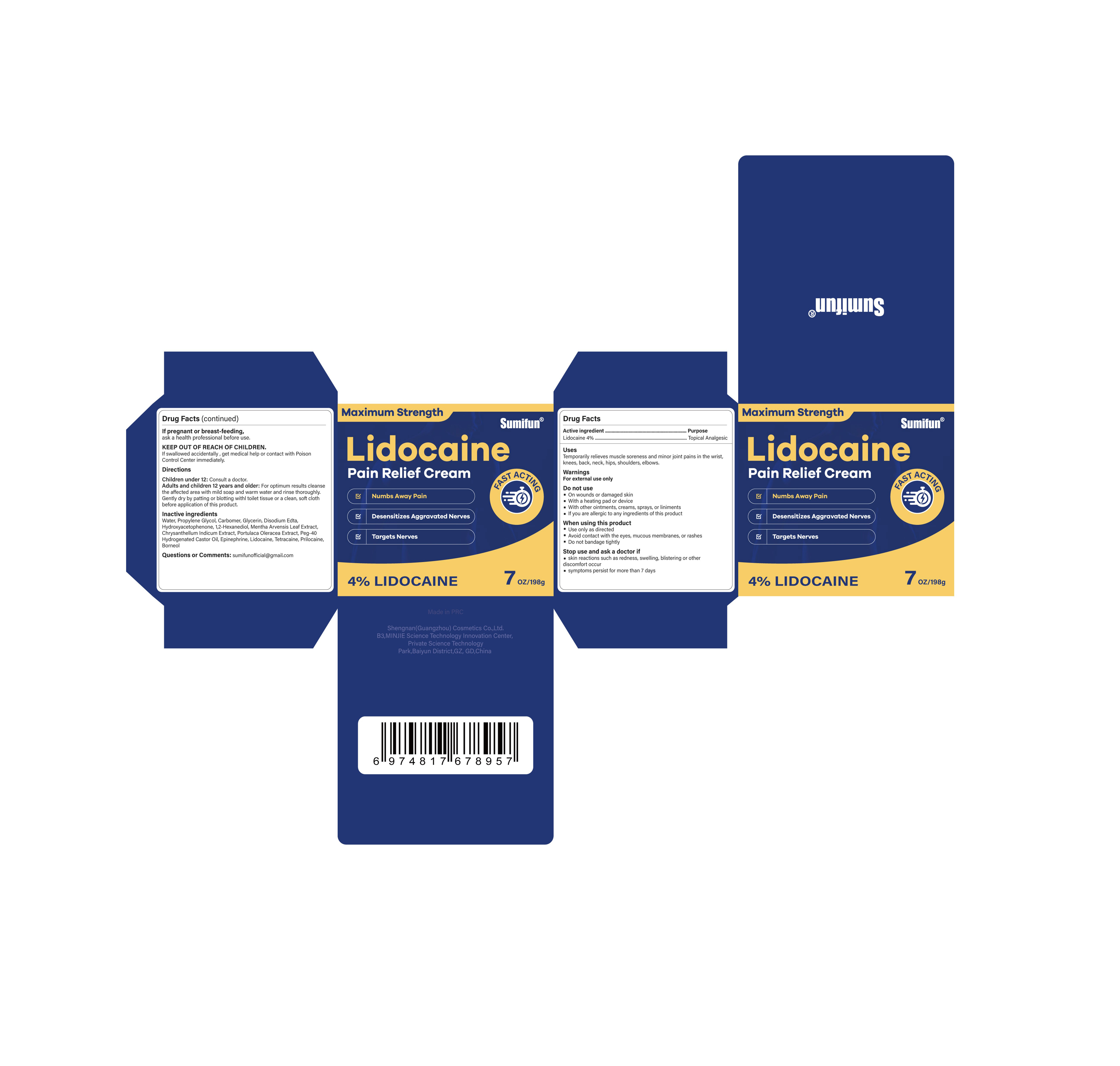 DRUG LABEL: Lidocaine Pain Relief Cream
NDC: 84019-101 | Form: CREAM
Manufacturer: Shengnan (Guangzhou) Cosmetics Co., LTD
Category: otc | Type: HUMAN OTC DRUG LABEL
Date: 20240124

ACTIVE INGREDIENTS: LIDOCAINE 4 g/100 g
INACTIVE INGREDIENTS: PEG-40 HYDROGENATED LANOLIN; WATER; PROPYLENE GLYCOL; MAGNESIUM DISODIUM EDTA; PORTULACA OLERACEA SEED; TETRACAINE; EPINEPHRINE; HYDROXYACETOPHENONE; MENTHA ARVENSIS LEAF; CHRYSANTHELLUM INDICUM TOP; GLYCERIN; 1,2-HEXANEDIOL; PRILOCAINE; BORNEOL; CARBOMER HOMOPOLYMER, UNSPECIFIED TYPE

Lidocaine Pain Relief Cream

Lidocaine Pain Relief Cream

ACTIVE INGREDIENT

LIDOCAINE 4%

PURPOSE

Topical Analgesic

INDICATIONS AND USAGE

Temporarily relieves muscle soreness and minor joint pains in the wrist, knees, back, neck, hips, shoulders, elbows.

WARNINGS

For external use only

DO NOT USE

On wounds or damaged skin
With a heating pad or device
With other ointments, creams, sprays, or liniments
If you are allergic to any ingredients of this product

WHEN USING

Use only as directed
Avoid contact with the eyes, mucous membranes, or rashes
Do not bandage tightly

STOP USE

skin reactions such as redness, swelling, blistering or other discomfort occur
symptoms persist for more than 7 days

KEEP OUT OF REACH OF CHILDREN

If swallowed accidentally , get medical help or contact with Poison Control Center immediately.

DOSAGE AND ADMINISTRATION

Children under 12: Consult a doctor.
Adults and children 12 years and older: For optimum results cleanse the affected area with mild soap and warm water and rinse thoroughly. Gently dry by patting or blotting withl toilet tissue or a clean, soft cloth before application of this product.

STORAGE AND HANDLING

Store in a dry and cool place

PREGNANCY OR BREAST FEEDING

ask a health professional before use.

INACTIVE INGREDIENT

Water
Propylene Glycol
Carbomer
Glycerin
Disodium Edta
Hydroxyacetophenone
1.2-Hexanediol
Mentha Arvensis Leaf Extract
Chrysanthellum Indicum Extract
Portulaca Oleracea Extract
Peg-40 Hydrogenated Castor Oil
Epinephrine
Tetracaine
Prilocaine
Borneol